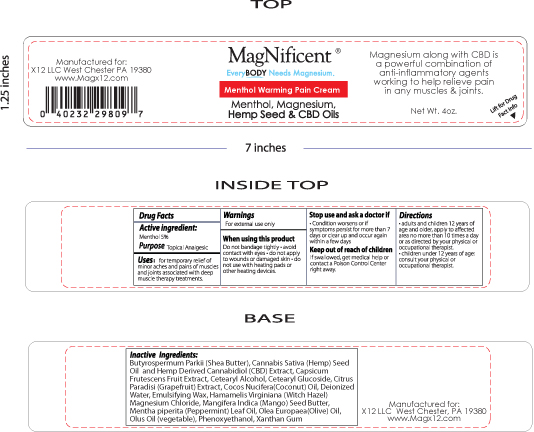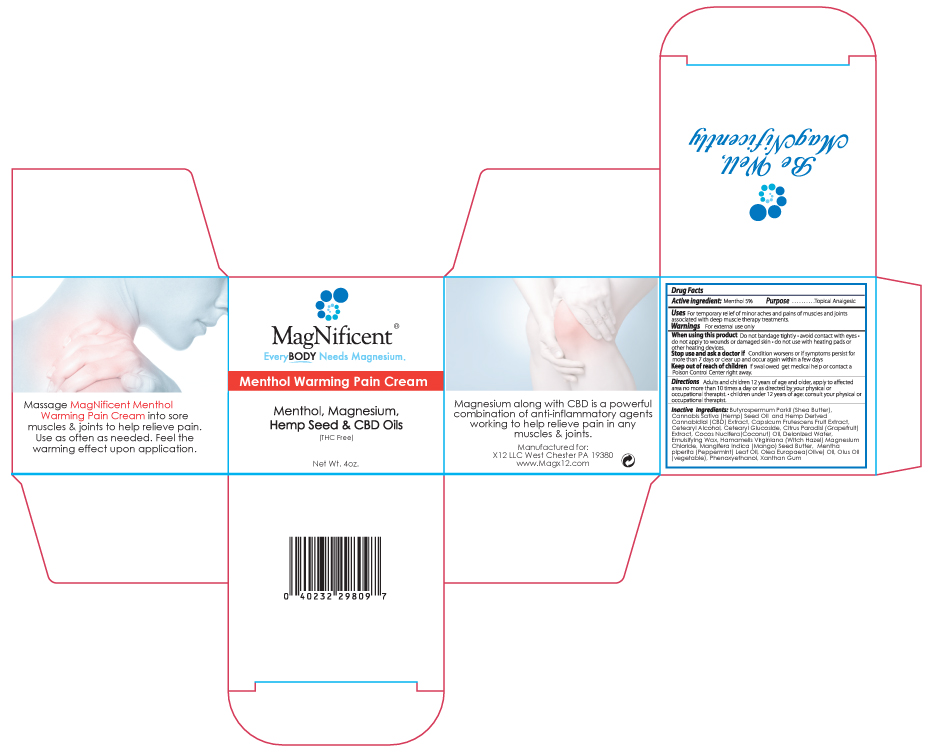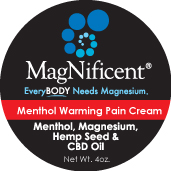 DRUG LABEL: MagNificent Menthol Warming Cream
NDC: 76348-422 | Form: CREAM
Manufacturer: RENU LABORATORIES, INC.
Category: otc | Type: HUMAN OTC DRUG LABEL
Date: 20220114

ACTIVE INGREDIENTS: MENTHOL 5.6 g/112 g
INACTIVE INGREDIENTS: WATER; XANTHAN GUM; CETOSTEARYL ALCOHOL; CETEARYL GLUCOSIDE; SHEA BUTTER; COCONUT OIL; MANGIFERA INDICA SEED BUTTER; OLIVE OIL; CANNABIDIOL; CANNABIS SATIVA SEED OIL; CORN OIL; WHITE WAX; PEPPERMINT OIL; CAPSICUM; GRAPEFRUIT OIL; MAGNESIUM CHLORIDE; WITCH HAZEL; C13-14 ISOPARAFFIN; PHENOXYETHANOL; LAURETH-7

MagNificent Menthol Warming Pain Cream

Active Ingredient:

Menthol 5%

PURPOSE

Topical Analgesic

Warnings

For external use only

When using this product

Do not bandage tightly

- avoid contact with eyes
- do not apply to wounds or damaged skin
- do not use with heating pads or other heating devices.

Stop use and ask a doctor if

- Condition worsens or if symptoms persist for more than 7 days or clear up and occur again within a few days

Keep out of reach of children

If swallowed, get medical help or contact a Poison Control Center right away.

Directions

adults and children 12 years of age and older, apply to affected area no more than 10 times a day or as directed by your physical or occupational therapist.
children under 12 years of age: consult your physical or occupational therapist.

Directions

- adults and children 12 years of age and older, apply to affected area no more than 10 times a day or as directed by your physical or occupational therapist.
- children under 12 years of age: consult your physical or occupational therapist.

Inactive Ingredients:

Butyrospermum Parkii (Shea) Butter, Cannabis Sativa (Hemp) Seed Oil and Hemp Oil and Hemp Derived Cannabidiol (CBD) Extract, Capsicum Frutescens Fruit Extract, Cetearyl Alcohol, Cetearyl Glucoside, Citrus Paradisi (Grapefruit) Extract, Cocos Nucifera (Coconut) Oil, Deionized Water, Emulsifying Wax, Hamamelis Virginiana (Witch Hazel), Magnesium Chloride, Mangifera Indica (Mango) Seed Butter, Mentha Piperita (Peppermint) Leaf Oil, Olea Europaea (Olive) Oil, Olus Oil (Vegetable), Phenoxyethanol, Xanthan Gum

QUESTIONS

Manufactured for:

X12LLC West Chester, PA 19380

www.Magx12.com

INDICATIONS AND USAGE

for temporary relief of minor aches and pains of muscles and joints associated with deep muscle therapy treatments

MAGNIFICENT_warming_Layered Label_FINALCorrected (2).jpg Magnificent_Round_Warming_CBD (2).jpg Magnificent-WARMING CBD_ART_Box_112718 (2).jpg

Magnificent_Round_Warming_CBD (2).jpg

MAGNIFICENT_warming_Layered Label_FINALCorrected (2).jpg